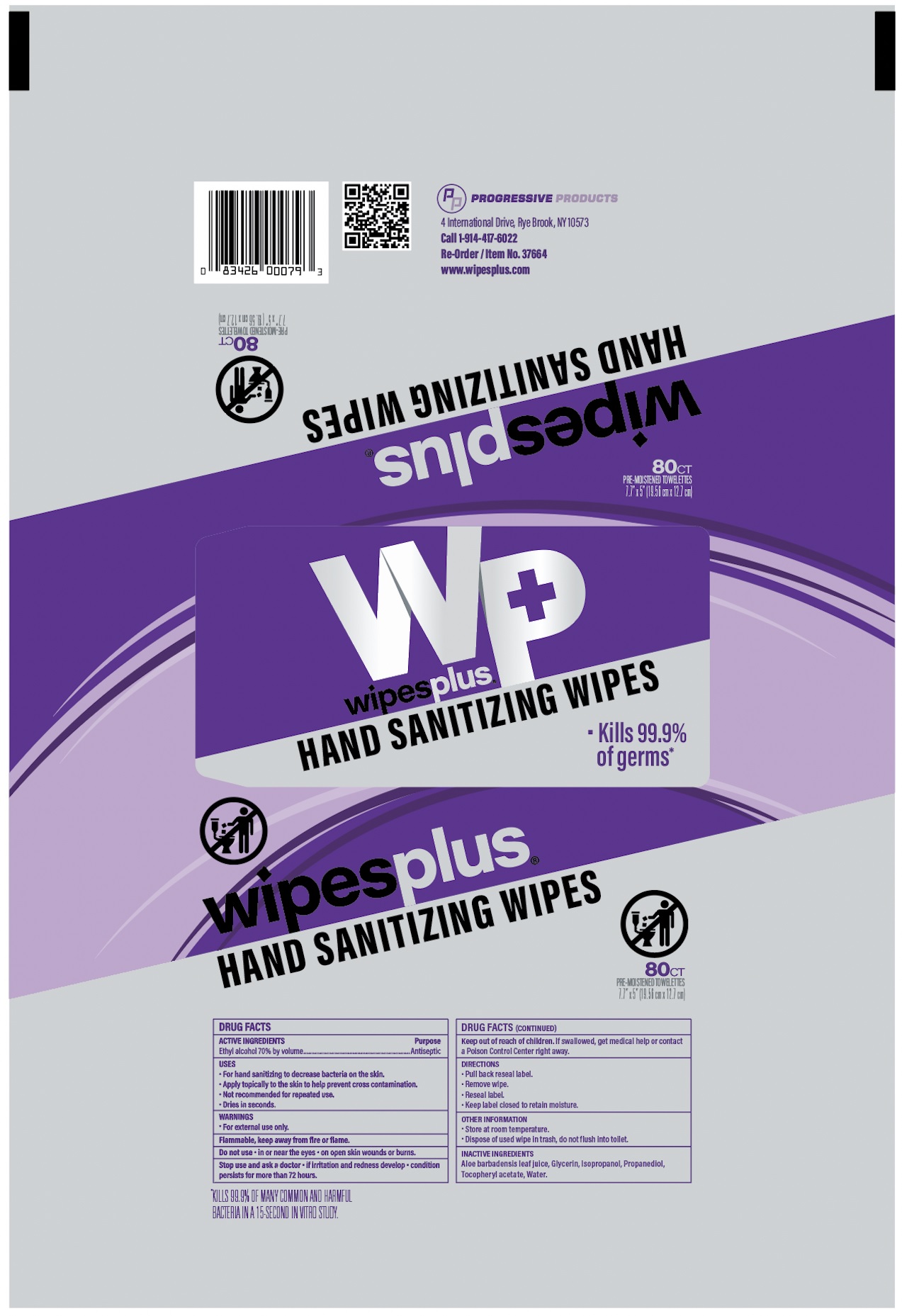 DRUG LABEL: Ethyl Alcohol
NDC: 67151-717 | Form: CLOTH
Manufacturer: Progressive
Category: otc | Type: HUMAN OTC DRUG LABEL
Date: 20221014

ACTIVE INGREDIENTS: ALCOHOL 70 mL/100 mL
INACTIVE INGREDIENTS: GLYCERIN; ISOPROPYL ALCOHOL; PROPANEDIOL; ALOE VERA LEAF; .ALPHA.-TOCOPHEROL ACETATE; WATER

Sanitizing Wipes - 80 ct

Active Ingredients

Ethyl alcohol 70% by volume

Purpose

Antiseptic

Uses

- For hand sanitizing to decrease bacteria on the skin.
- Apply topically to the skin to help prevent cross contamination.
- Not recommended for repeated use.
- Dries in seconds.

Warnings

- For external use only.

Do not use

- in or near the eyes
- on open skin wounds or burns

Stop use and ask a doctor

- if irritation and redness develop
- condition persists for more than 72 hours.

Directions

- Pull back reseal label.
- Remove wipe.
- Reseal label.
- Keep label closed to retain moisture.

Other Information

- Store at room temperature.
- Dispose of used wipe in trash, do not flush into toilet.

Inactive Ingredients

Aloe barbadensis leaf juic, Glycerin, Isopropanol, Propanediol, Tocopheryl acetate, Water.

Keep out of reach of children.

If swallowed, get medical help or contact a Poison Control Center right away.

Principal Display Panel

wipesplu

HAND SANITIZING WIPES

- Kills 99.9% of germs

80CT

PRE-MOISTENED TOWELETTES